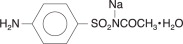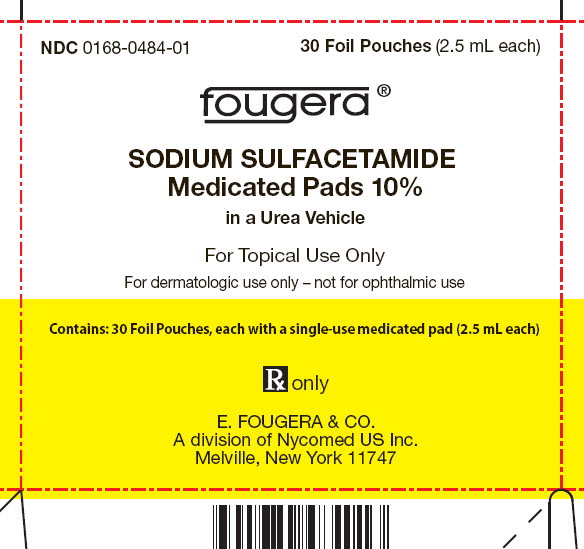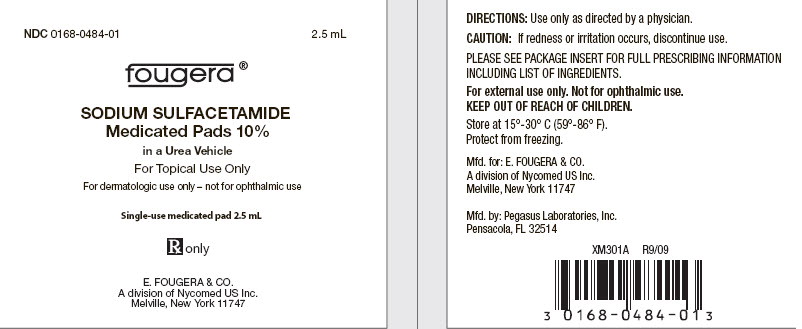 DRUG LABEL: Sodium Sulfacetamide
NDC: 0168-0484 | Form: SOLUTION
Manufacturer: E. FOUGERA & Co., A division of Nycomed  US Inc.
Category: prescription | Type: HUMAN PRESCRIPTION DRUG LABEL
Date: 20100312

ACTIVE INGREDIENTS: sulfacetamide sodium 100 mg/1 g
INACTIVE INGREDIENTS: water; sodium thiosulfate; urea

SODIUM SULFACETAMIDE Medicated Pads 10%

in a Urea Vehicle

FOR DERMATOLOGIC USE ONLY

Rx only

NOT FOR OPHTHALMIC USE

DESCRIPTION:

Sodium Sulfacetamide Medicated Pads 10% contain a 10% solution of sodium sulfacetamide on a textured pad. Each gram of medicated solution contains 100 mg sodium sulfacetamide, purified water, sodium EDTA, sodium thiosulfate and urea (1 0%). Sodium Sulfacetamide Medicated Pads are greaseless and leave no residue when applied to the skin.

Sodium sulfacetamide is a sulfonamide with antibacterial activity. Chemically, sodium sulfacetamide is C8H9N2Na03S•H2O, with a molecular weight of 254.24. Chemically it is acetamide, N- [(4 aminophenyl) sulfonyl]-, monosodium salt and monohydrate, with the following structural formula:

CLINICAL PHARMACOLOGY:

Sodium sulfacetamide exerts a bacteriostatic effect against sulfonamide-sensitive gram-positive and gram-negative micro-organism including P. acne commonly isolasted from secondary cutaneous pyogenic infections.

The most widely accepted mechanism of action of sulfonamides is the Woods-Fildes theory, which is based on the fact that sulfonamides act as competitive antagonists to para-aminobenzoic acid P (ABA), an essential component for bacterial growth. While absorption through intact skin in humans has not been determined, sodium sulfacetamide is readily absorbed from the gastrointestinal tract when taken orally and excreted in the urine largely unchanged. The biological half-life has variously been reported as 7 o t 12.8 hours.

INDICATIONS AND USAGE:

Sodium Sulfacetamide Medicated Pads are indicated in the topical control of acne vulgaris, acne rosacea and seborrheic dermatitis.

CONTRAINDICATIONS:

Sodium Sulfacetamide Medicated Pads are contraindicated in persons with known or suspected hypersensitivity to sulfonamides or to any of the ingredients of the preparation. Sodium Sulfacetamide Medicated Pads are not to be used by patients with kidney disease.

WARNINGS:

Although rare, sensitivity t o sodium sulfacetamide may occur. Therefore, caution and careful supervision should be observed when prescribing this drug for patients who may be prone to hypersensitivity to topical sulfonamides. Systemic toxic reactions such as agranulocytosis, acute hemolytic anemia, purpura hemorrhagica, drug fever, jaundice, and contact dermatitis indicate hypersensitivity to sulfonamides. Sulfonamides are known to cause Stevens-Johnson syndrome in hypersensitive individuals. Stevens-Johnson syndrome also has been reported following the use of sodium sulfacetamide topically. Cases of drug-induced systemic lupus erythematosus from topical sulfacetamide also have been reported.

PRECAUTIONS:

GENERAL PRECAUTIONS

General: Nonsusceptible organisms, including fungi, may proliferate with the use of this preparation. Hypersensitivity reactions may recur when a sulfonamide is readministered, irrrespective of the route of administration, and cross hypersensitivity between different sulfonamides may occur. If Sodium Sulfacetamide Medicated Pads produce signs of hypersensitivity or other untoward reactions, discontinue use of the preparation. Systemic absorption of topical sulfonamides is greater following application to large, infected, abraded, denuded, or severely burned areas. Under these circumstances, potentially any of the adverse effects produced by the systemic administration of these agents could occur, and appropriate observations and laboratory determinations should be performed.

INFORMATION FOR PATIENTS:

Avoid contact with eyes, eyelids, lips and mucous membranes. If accidental contact occurs, rinse with water. Patients should discontinue the use of Sodium Sulfacetamide Medicated Pads if the condition becomes worse, or if a rash develops in the area being treated or elsewhere. Sodium Sulfacetamide Medicated Pads also should be discontinued promptly and the physician notified if any arthritis, fever, or sores in the mouth develop.

DRUG INTERACTIONS

Drug Interactions: Sodium Sulfacetamide Medicated Pads are incompatible with silver preparations.

CARCINOGENESIS AND MUTAGENESIS AND IMPAIRMENT OF FERTILITY

Carcinogenesis, Mutagenesis, and Impairment of Fertility: Long-term animal studies for carcinogenic potential have not been performed on Sodium Sulfacetamide Medicated Pads.

PREGNANCY

Pregnancy Category C: Animal reproduction studies have not been conducted with Sodium Sulfacetamide Medicated Pads. It also is not known whether Sodium Sulfacetamide Medicated Pads can cause fetal harm when administered to a pregnant woman or can affect reproduction capacity. Sodium Sulfacetamide Medicated Pads should be used by a pregnant woman only if clearly needed.

NURSING MOTHERS

Nursing Mothers: It is not known whether this drug is excreted in human milk following topical use of Sodium Sulfacetamide Medicated Pads. Because many drugs are excreted in human milk, caution should be exercised when Sodium Sulfacetamide Medicated Pads are administered to a nursing woman.

PEDIATRIC USE

Pediatric Use: Safety and effectiveness in children below the age of 12 years have not been established.

ADVERSE REACTIONS:

Reports of irritation and hypersensitivity to sodium sulfacetamide are uncommon. The following adverse reactions, reported after administration of sterile ophthalmic sodium sulfacetamide, are noteworthy: instances of Stevens-Johnson syndrome and instances of local hypersensitivity, which progressed to a syndrome resembling systemic lupus erythematosus; in one case a fatal outcome has been reported (see WARNINGS).

DOSAGE AND ADMINISTRATION:

Gently apply Sodium Sulfacetamide Medicated Pads to the affected areas 1 to 2 times daily or as directed by a physician until the infection has cleared.

HOW SUPPLIED:

Sodium Sulfacetamide Medicated Pads NDC 0168-0484-01 contain 30 Foil Pouches, each with a single-use medicated pad (2.5 mL each).

Store at 15°-30° C (59°-86° F). Protect from freezing.

Sodium Sulfacetamide Medicated Pads may darken after prolonged storage. Slight discoloration does not impair the efficacy or safety of the product.

Manufactured for: E. FOUGERA & CO.
A division of Nycomed US Inc., Melville New York 11747
Manufactured by: Pegasus Laboratories, Inc., Pensacola, FL 32514

IL302A R3/09

PACKAGE LABEL – PRINCIPAL DISPLAY PANEL – CARTON – 30 CT

NDC 0168-0484-01

30 Foil Pouches (2.5 mL each)

Fougera®

SODIUM SULFACETAMIDE

Medicated Pads 10%

In a Urea Vehicle

For Topical Use Only

For dermatologic use only – not for ophthalmic use

Contains: 30 Foil Pouches, each with a single-use medicated pad (2.5 mL each)

Rx only

E. FOUGERA & CO.

A division of Nycomed US Inc.

Melville, New York 11747

PACKAGE LABEL – PRINCIPAL DISPLAY PANEL – CONTAINER – 2.5 mL

NDC 0168-0484-01

2.5 mL

Fougera®

SODIUM SULFACETAMIDE

Medicated Pads 10%

in a Urea Vehicle

For Topical Use Only

For dermatologic use only – not for ophthalmic use

Single-use medicated pad 2.5 mL

Rx only

E. FOUGERA & CO.

A division of Nycomed US Inc.

Melville, New York 11747